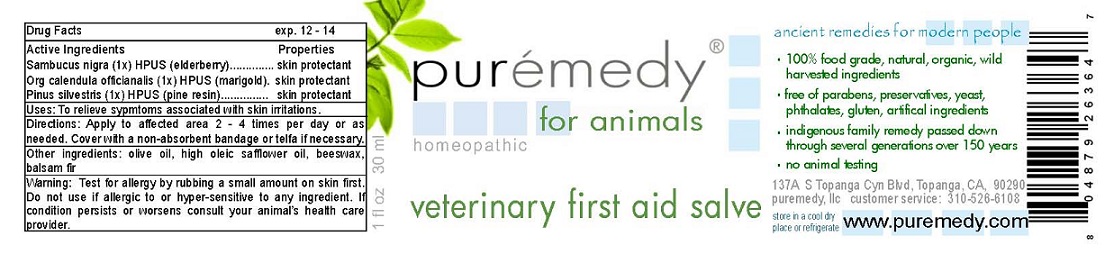 DRUG LABEL: VETERNIARY FIRST AID
NDC: 52810-205 | Form: SALVE
Manufacturer: PUREMEDY
Category: homeopathic | Type: HUMAN OTC DRUG LABEL
Date: 20121029

ACTIVE INGREDIENTS: SAMBUCUS NIGRA FLOWER 1 [hp_X]/100 mL; CALENDULA OFFICINALIS FLOWER 1 [hp_X]/100 mL; PINE NEEDLE OIL (PINUS SYLVESTRIS) 1 [hp_X]/100 mL
INACTIVE INGREDIENTS: OLIVE OIL; SAFFLOWER OIL; YELLOW WAX; ABIES BALSAMEA LEAF OIL

ACTIVE INGREDIENTS

SAMBUCUS NIGRA (1X) HPUS (ELDERBERRY)

ORG. CALENDULA (1X) HPUS (MARIGOLD)

PINUS SYLVESTRIS (1X) HPUS (PINE RESIN)

PURPOSE

PROPERTIES

SKIN PROTECTANT

SKIN PROTECTANT

SKIN PROTECTANT

INDICATIONS AND USAGE

USES: TO RELIEVE SYMPTOMS ASSOCIATED WITH SKIN IRRITATIONS.

DOSAGE AND ADMINISTRATION

DIRECTIONS: APPLY TO AFFECTED AREA 2-4 TIMES PER DAY OR AS NEEDED. COVER WITH NON-ABSORBENT BANDAGE OR TELFA IF NECESSARY.

INACTIVE INGREDIENT

OTHER INGREDIENTS: OLIVE OIL, HIGH OLEIC SAFFLOWER OIL, BEESWAX, BALSAM FIR

WARNINGS

WARNING: TEST FOR ALLERGY BY RUBBING A SMALL AMOUNT ON SKIN FIRST. DO NOT USE IF ALLERGIC TO OR HYPER-SENSITIVE TO ANY INGREDIENT IN THIS SALVE. IF CONDITION PERSISTS OR WORSENS CONSULT YOUR HEALTH CARE PROVIDER. (* = CERTIFIED ORGANIC INGREDIENTS)

KEEP OUT OF REACH OF CHILDREN.

QUESTIONS

CUSTOMER SERVICE: 310-526-6108